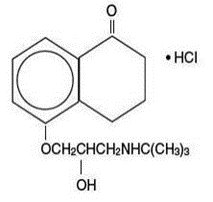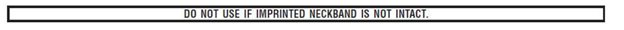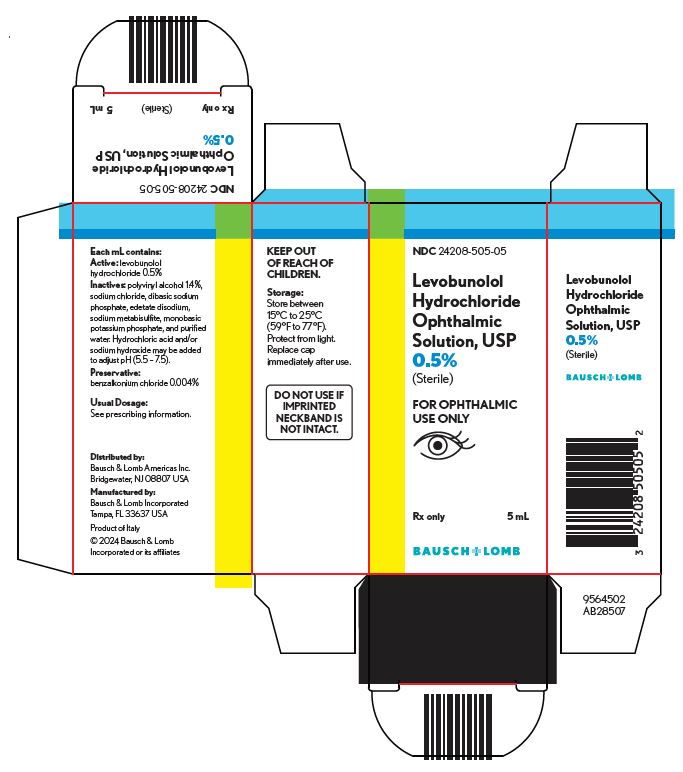 DRUG LABEL: Levobunolol Hydrochloride
NDC: 24208-505 | Form: SOLUTION/ DROPS
Manufacturer: Bausch & Lomb Incorporated
Category: prescription | Type: HUMAN PRESCRIPTION DRUG LABEL
Date: 20240724

ACTIVE INGREDIENTS: LEVOBUNOLOL HYDROCHLORIDE 5 mg/1 mL
INACTIVE INGREDIENTS: BENZALKONIUM CHLORIDE 0.04 mg/1 mL; POLYVINYL ALCOHOL, UNSPECIFIED 14 mg/1 mL; SODIUM CHLORIDE; EDETATE DISODIUM; SODIUM METABISULFITE; MONOBASIC POTASSIUM PHOSPHATE; WATER; HYDROCHLORIC ACID; SODIUM HYDROXIDE

Levobunolol Hydrochloride
Ophthalmic Solution, USP
0.5%
(Sterile)
Rx only
FOR USE IN THE EYES ONLY

DESCRIPTION

Levobunolol hydrochloride ophthalmic solution USP, 0.5% is a noncardioselective beta-adrenoceptor blocking agent for ophthalmic use.

Levobunolol hydrochloride is represented by the following structural formula:

Mol. Formula C17H25NO3•HCl

Mol. Wt. 327.85

Chemical Name:(–)-5-[3-(tert-Butylamino)-2-hydroxypropoxy]-3,4-dihydro-1(2 H)- naphthalenone hydrochloride.

Each mL of 0.5% contains:

Active:levobunolol hydrochloride 0.5%; Inactives:polyvinyl alcohol 1.4%, sodium chloride, dibasic sodium phosphate, edetate disodium, sodium metabisulfite, monobasic potassium phosphate, and purified water. Hydrochloric acid and/or sodium hydroxide may be added to adjust pH (5.5 - 7.5); Preservative:benzalkonium chloride (0.004%).

CLINICAL PHARMACOLOGY

Levobunolol hydrochloride is a noncardioselective beta-adrenoceptor blocking agent, equipotent at both beta1and beta2receptors. Levobunolol hydrochloride is greater than 60 times more potent than its dextro isomer in its beta-blocking activity, yet equipotent in its potential for direct myocardial depression. Accordingly, the levo isomer, levobunolol hydrochloride, is used. Levobunolol hydrochloride does not have significant local anesthetic (membrane-stabilizing) or intrinsic sympathomimetic activity.

Beta-adrenergic receptor blockade reduces cardiac output in both healthy subjects and patients with heart disease. In patients with severe impairment of myocardial function, beta-adrenergic receptor blockade may inhibit the stimulatory effect of the sympathetic nervous system necessary to maintain adequate cardiac function.

Beta-adrenergic receptor blockade in the bronchi and bronchioles results in increased airway resistance from unopposed parasympathetic activity. Such an effect in patients with asthma or other bronchospastic conditions is potentially dangerous.

Levobunolol hydrochloride ophthalmic solution, USP has been shown to be an active agent in lowering elevated as well as normal intraocular pressure (IOP) whether or not accompanied by glaucoma. Elevated IOP presents a major risk factor in glaucomatous field loss. The higher the level of IOP, the greater the likelihood of optic nerve damage and visual field loss.

The onset of action with one drop of levobunolol hydrochloride ophthalmic solution can be detected within one hour after treatment, with maximum effect seen between 2 and 6 hours.

A significant decrease in IOP can be maintained for up to 24 hours following a single dose.

In controlled clinical studies of approximately two years duration, intraocular pressure was well-controlled in approximately 80% of subjects treated with levobunolol hydrochloride ophthalmic solution 0.5% twice a day. The mean IOP decrease from baseline was between 7 mm Hg and 8 mm Hg. No significant effects on pupil size, tear production or corneal sensitivity were observed. Levobunolol hydrochloride ophthalmic solution at the concentrations tested, when applied topically, decreased heart rate and blood pressure in some patients. The IOP-lowering effect of levobunolol hydrochloride ophthalmic solution was well maintained over the course of these studies.

In a three-month clinical study, a single daily application of 0.5% levobunolol hydrochloride ophthalmic solution controlled the IOP of 72% of subjects achieving an overall mean decrease in IOP of 7.0 mm Hg.

The primary mechanism of the ocular hypotensive action of levobunolol hydrochloride in reducing IOP is most likely a decrease in aqueous humor production. Levobunolol hydrochloride ophthalmic solution reduces IOP with little or no effect on pupil size or accommodation.

INDICATIONS AND USAGE

Levobunolol hydrochloride ophthalmic solution has been shown to be effective in lowering intraocular pressure and may be used in patients with chronic open-angle glaucoma or ocular hypertension.

CONTRAINDICATIONS

Levobunolol hydrochloride ophthalmic solution is contraindicated in those individuals with bronchial asthma, or with a history of bronchial asthma, or severe chronic obstructive pulmonary disease (see WARNINGS); sinus bradycardia; second and third degree atrioventricular block; overt cardiac failure (see WARNINGS); cardiogenic shock; or hypersensitivity to any component of these products.

WARNINGS

As with other topically applied ophthalmic drugs, levobunolol hydrochloride ophthalmic solution may be absorbed systemically. The same adverse reactions found with systemic administration of beta-adrenergic blocking agents may occur with topical administration. For example, severe respiratory reactions and cardiac reactions, including death due to bronchospasm in patients with asthma, and rarely death in association with cardiac failure, have been reported with topical application of beta-adrenergic blocking agents (see CONTRAINDICATIONS). Additionally, ophthalmic beta-blockers may impair compensatory tachycardia and increase risk of hypotension.

Cardiac Failure

Sympathetic stimulation may be essential for support of the circulation in individuals with diminished myocardial contractility, and its inhibition by beta-adrenergic receptor blockade may precipitate more severe failure.

In Patients Without a History of Cardiac Failure

Continued depression of the myocardium with beta-blocking agents over a period of time can, in some cases, lead to cardiac failure. At the first sign or symptom of cardiac failure, levobunolol hydrochloride ophthalmic solution should be discontinued (see CONTRAINDICATIONS).

Potentiation of Vascular Insufficiency

Levobunolol hydrochloride ophthalmic solution may potentiate syndromes associated with vascular insufficiency (i.e. Raynaud’s phenomenon), and therefore, should be used with caution in these patients.

Obstructive Pulmonary Disease

PATIENTS WITH CHRONIC OBSTRUCTIVE PULMONARY DISEASE (e.g., CHRONIC BRONCHITIS, EMPHYSEMA) OF MILD OR MODERATE SEVERITY, BRONCHOSPASTIC DISEASE OR A HISTORY OF BRONCHOSPASTIC DISEASE (OTHER THAN BRONCHIAL ASTHMA OR A HISTORY OF BRONCHIAL ASTHMA, IN WHICH LEVOBUNOLOL HYDROCHLORIDE OPHTHALMIC SOLUTION IS CONTRAINDICATED, SEE CONTRAINDICATIONS), SHOULD IN GENERAL NOT RECEIVE BETA BLOCKERS, INCLUDING LEVOBUNOLOL HYDROCHLORIDE OPHTHALMIC SOLUTION. However, if levobunolol hydrochloride ophthalmic solution is deemed necessary in such patients, then it should be administered cautiously since it may block bronchodilation produced by endogenous and exogenous catecholamine stimulation of beta2receptors.

Major Surgery

The necessity or desirability of withdrawal of beta-adrenergic blocking agents prior to major surgery is controversial. Beta-adrenergic receptor blockade impairs the ability of the heart to respond to beta-adrenergically mediated reflex stimuli. This may augment the risk of general anesthesia in surgical procedures. Some patients receiving beta-adrenergic receptor blocking agents have been subject to protracted severe hypotension during anesthesia. Difficulty in restarting and maintaining the heartbeat has also been reported. For these reasons, in patients undergoing elective surgery, gradual withdrawal of beta-adrenergic blocking agents may be appropriate.

If necessary during surgery, the effects of beta-adrenergic blocking agents may be reversed by sufficient doses of such agonists as isoproterenol, dopamine, dobutamine or levarterenol (see OVERDOSAGE).

Diabetes Mellitus

Beta-adrenergic blocking agents should be administered with caution in patients subject to spontaneous hypoglycemia or to diabetic patients (especially those with labile diabetes) who are receiving insulin or oral hypoglycemic agents. Beta-adrenergic blocking agents may mask the signs and symptoms of acute hypoglycemia.

Thyrotoxicosis

Beta-adrenergic blocking agents may mask certain clinical signs (e.g., tachycardia) of hyperthyroidism. Patients suspected of developing thyrotoxicosis should be managed carefully to avoid abrupt withdrawal of beta-adrenergic blocking agents which might precipitate a thyroid storm.

Choroidal Detachment

Choroidal detachment after filtration procedures has been reported with the administration of aqueous suppressant therapy.

These products contain sodium metabisulfite, a sulfite that may cause allergic-type reactions including anaphylactic symptoms and life-threatening or less severe asthmatic episodes in certain susceptible people. The overall prevalence of sulfite sensitivity in the general population is unknown and probably low. Sulfite sensitivity is seen more frequently in asthmatic than in nonasthmatic people.

PRECAUTIONS

General

Levobunolol hydrochloride ophthalmic solution, USP should be used with caution in patients with known hypersensitivity to other beta-adrenoceptor blocking agents.

Use with caution in patients with known diminished pulmonary function.

Levobunolol hydrochloride ophthalmic solution should be used with caution in patients who are receiving a beta-adrenergic blocking agent orally, because of the potential for additive effects on systemic beta-blockade or on intraocular pressure. Patients should not typically use two or more topical ophthalmic beta-adrenergic blocking agents simultaneously.

Because of the potential effects of beta-adrenergic blocking agents on blood pressure and pulse rates, these medications must be used cautiously in patients with cerebrovascular insufficiency. Should signs or symptoms develop that suggest reduced cerebral blood flow while using levobunolol hydrochloride ophthalmic solution, alternative therapy should be considered.

In patients with angle-closure glaucoma, the immediate objective of treatment is to reopen the angle. This requires, in most cases, constricting the pupil with a miotic. Levobunolol hydrochloride ophthalmic solution has little or no effect on the pupil. When levobunolol hydrochloride ophthalmic solution is used to reduce elevated intraocular pressure in angle-closure glaucoma, it should be followed with a miotic and not alone.

The preservative in levobunolol hydrochloride ophthalmic solution, benzalkonium chloride, may be absorbed by soft contact lenses. Patients wearing soft (hydrophilic) contact lenses should be instructed to remove contact lenses before administration of the solution and wait at least 15 minutes after instilling levobunolol hydrochloride ophthalmic solution before reinserting soft contact lenses.

Muscle Weakness

Beta-adrenergic blockade has been reported to potentiate muscle weakness consistent with certain myasthenic symptoms (e.g., diplopia, ptosis and generalized weakness).

Drug Interactions

Although levobunolol hydrochloride ophthalmic solution used alone has little or no effect on pupil size, mydriasis resulting from concomitant therapy with levobunolol hydrochloride ophthalmic solution and epinephrine may occur.

Close observation of the patient is recommended when a beta-blocker is administered to patients receiving catecholamine-depleting drugs such as reserpine, because of possible additive effects and the production of hypotension and/or marked bradycardia, which may produce vertigo, syncope, or postural hypotension.

Patients receiving beta-adrenergic blocking agents along with either oral or intravenous calcium antagonists should be monitored for possible atrioventricular conduction disturbances, left ventricular failure and hypotension. In patients with impaired cardiac function, simultaneous use should be avoided altogether.

The concomitant use of beta-adrenergic blocking agents with digitalis and calcium antagonists may have additive effects on prolonging atrioventricular conduction time.

Phenothiazine-related compounds and beta-adrenergic blocking agents may have additive hypotensive effects due to the inhibition of each other’s metabolism.

Risk of Anaphylactic Reaction

While taking beta-blockers, patients with a history of severe anaphylactic reactions to a variety of allergens may be more reactive to repeated challenge, either accidental, diagnostic, or therapeutic. Such patients may be unresponsive to the usual doses of epinephrine used to treat allergic reactions.

Carcinogenesis, Mutagenesis, Impairment of Fertility

In a lifetime oral study in mice, there were statistically significant (p≤0.05) increases in the incidence of benign leiomyomas in female mice at 200 mg/kg/day (14,000 times the recommended human dose for glaucoma), but not at 12 or 50 mg/kg/day (850 and 3,500 times the human dose). In a two year oral study of levobunolol hydrochloride in rats, there was a statistically significant (p≤0.05) increase in the incidence of benign hepatomas in male rats administered 12,800 times the recommended human dose for glaucoma. Similar differences were not observed in rats administered oral doses equivalent to 350 times to 2,000 times the recommended human dose for glaucoma.

Levobunolol did not show evidence of mutagenic activity in a battery of microbiological and mammalian in vitroand in vivoassays.

Reproduction and fertility studies in rats showed no adverse effect on male or female fertility at doses up to 1,800 times the recommended human dose for glaucoma.

Pregnancy

Fetotoxicity (as evidenced by a greater number of resorption sites) has been observed in rabbits when doses of levobunolol hydrochloride equivalent to 200 and 700 times the recommended dose for the treatment of glaucoma were given. No fetotoxic effects have been observed in similar studies with rats at up to 1,800 times the human dose for glaucoma. Teratogenic studies with levobunolol in rats at doses up to 25 mg/kg/day (1,800 times the recommended human dose for glaucoma) showed no evidence of fetal malformations. There were no adverse effects on postnatal development of offspring. It appears when results from studies using rats and studies with other beta-adrenergic blockers are examined, that the rabbit may be a particularly sensitive species. There are no adequate and well-controlled studies in pregnant women. Levobunolol hydrochloride ophthalmic solution should be used during pregnancy only if the potential benefit justifies the potential risk to the fetus.

Nursing Mothers

It is not known whether this drug is excreted in human milk. Systemic beta-blockers and topical timolol maleate are known to be excreted in human milk. Caution should be exercised when levobunolol hydrochloride ophthalmic solution is administered to a nursing woman.

Pediatric Use

Safety and effectiveness in pediatric patients have not been established.

Geriatric Use

No overall differences in safety or effectiveness have been observed between elderly and younger patients.

ADVERSE REACTIONS

In clinical trials the use of levobunolol hydrochloride ophthalmic solution has been associated with transient ocular burning and stinging in up to 1 in 3 patients, and with blepharoconjunctivitis in up to 1 in 20 patients. Decreases in heart rate and blood pressure have been reported (see CONTRAINDICATIONSand WARNINGS).

The following adverse reactions have been reported rarely with the use of levobunolol hydrochloride ophthalmic solution: iridocyclitis, headache, transient ataxia, dizziness, lethargy, urticaria, and pruritus.

Decreased corneal sensitivity has been noted in a small number of patients. Although levobunolol has minimal membrane-stabilizing activity, there remains a possibility of decreased corneal sensitivity after prolonged use.

The following additional adverse reactions have been reported either with levobunolol hydrochloride ophthalmic solution or ophthalmic use of other beta-adrenergic receptor blocking agents:

BODY AS A WHOLE:Headache, asthenia, chest pain. CARDIOVASCULAR:Bradycardia, arrhythmia, hypotension, syncope, heart block, cerebral vascular accident, cerebral ischemia, congestive heart failure, palpitation, cardiac arrest. DIGESTIVE:Nausea, diarrhea. PSYCHIATRIC:Depression, confusion, increase in signs and symptoms of myasthenia gravis, paresthesia. SKIN:Hypersensitivity, including localized and generalized rash, alopecia, Stevens-Johnson Syndrome. RESPIRATORY:Bronchospasm (predominantly in patients with pre-existing bronchospastic disease), respiratory failure, dyspnea, nasal congestion. UROGENITAL:Impotence. ENDOCRINE:Masked symptoms of hypoglycemia in insulin-dependent diabetics (see WARNINGS). SPECIAL SENSES:Signs and symptoms of keratitis or eye allergy, blepharoptosis, visual disturbances including refractive changes (due to withdrawal of miotic therapy in some cases), diplopia, ptosis, and foreign body sensation in eye.

Other reactions associated with the oral use of non-selective adrenergic receptor blocking agents should be considered potential effects with ophthalmic use of these agents.

To report SUSPECTED ADVERSE REACTIONS, contact Bausch & Lomb Incorporated at
1-800-553-5340 or FDA at 1-800-FDA-1088 or www.fda.gov/medwatch.

OVERDOSAGE

No data are available regarding overdosage in humans. Should accidental ocular overdosage occur, flush eye(s) with water or normal saline. If accidentally ingested, efforts to decrease further absorption may be appropriate (gastric lavage). The most common signs and symptoms to be expected with overdosage with administration of a systemic beta-adrenergic blocking agent are symptomatic bradycardia, hypotension, bronchospasm, and acute cardiac failure. Should these symptoms occur, discontinue levobunolol hydrochloride ophthalmic solution therapy and initiate appropriate supportive therapy. The following supportive measures should be considered:

1. Symptomatic bradycardia: Use atropine sulfate intravenously in a dosage of 0.25 mg to 2 mg to induce vagal blockade. If bradycardia persists, intravenous isoproterenol hydrochloride should be administered cautiously. In refractory cases the use of a transvenous cardiac pacemaker should be considered.

2. Hypotension: Use sympathomimetic pressor drug therapy, such as dopamine, dobutamine or levarterenol. In refractory cases the use of glucagon hydrochloride may be useful.

3. Bronchospasm: Use isoproterenol hydrochloride. Additional therapy with aminophylline may be considered.

4. Acute cardiac failure: Conventional therapy with digitalis, diuretics and oxygen should be instituted immediately. In refractory cases the use of intravenous aminophylline is suggested. This may be followed, if necessary, by glucagon hydrochloride which may be useful.

5. Heart block (second or third degree): Use isoproterenol hydrochloride or a transvenous cardiac pacemaker.

DOSAGE AND ADMINISTRATION

The recommended starting dose is one to two drops of levobunolol hydrochloride ophthalmic solution, 0.5% in the affected eye(s) once a day. In patients with more severe or uncontrolled glaucoma, levobunolol hydrochloride ophthalmic solution, 0.5% can be administered twice a day. As with any new medication, careful monitoring of patients is advised. Dosages above one drop of levobunolol hydrochloride ophthalmic solution, 0.5% twice a day are not generally more effective. If the patient's IOP is not at a satisfactory level on this regimen, concomitant therapy with other ophthalmic IOP-lowering agents can be instituted. Patients should not typically use two or more topical ophthalmic beta-adrenergic blocking agents simultaneously.

HOW SUPPLIED

Levobunolol hydrochloride ophthalmic solution USP, 0.5% is supplied sterile in a plastic bottle with a controlled drop tip in the following sizes:

NDC 24208-505-05 - 5 mL

NDC 24208-505-10 - 10 mL

NDC 24208-505-15 - 15 mL

Storage:Store between 15°C to 25°C (59°F to 77°F). Protect from light. Replace cap immediately after use.

KEEP OUT OF REACH OF CHILDREN.

Distributed by:
Bausch & Lomb Americas Inc.
Bridgewater, NJ 08807 USA

Manufactured by:
Bausch & Lomb Incorporated
Tampa, FL 33637 USA

© 2022 Bausch & Lomb Incorporated or its affiliates

Revised: October 2022

9117404 (Folded)

9117504 (Flat)

PACKAGE/LABEL PRINCIPAL DISPLAY PANEL

NDC 24208-505-05

Levobunolol
Hydrochloride
Ophthalmic
Solution, USP
0.5%
(Sterile)

FOR OPHTHALMIC
USE ONLY.

Rx only

5 mL

BAUSCH + LOMB

9564502
AB28507